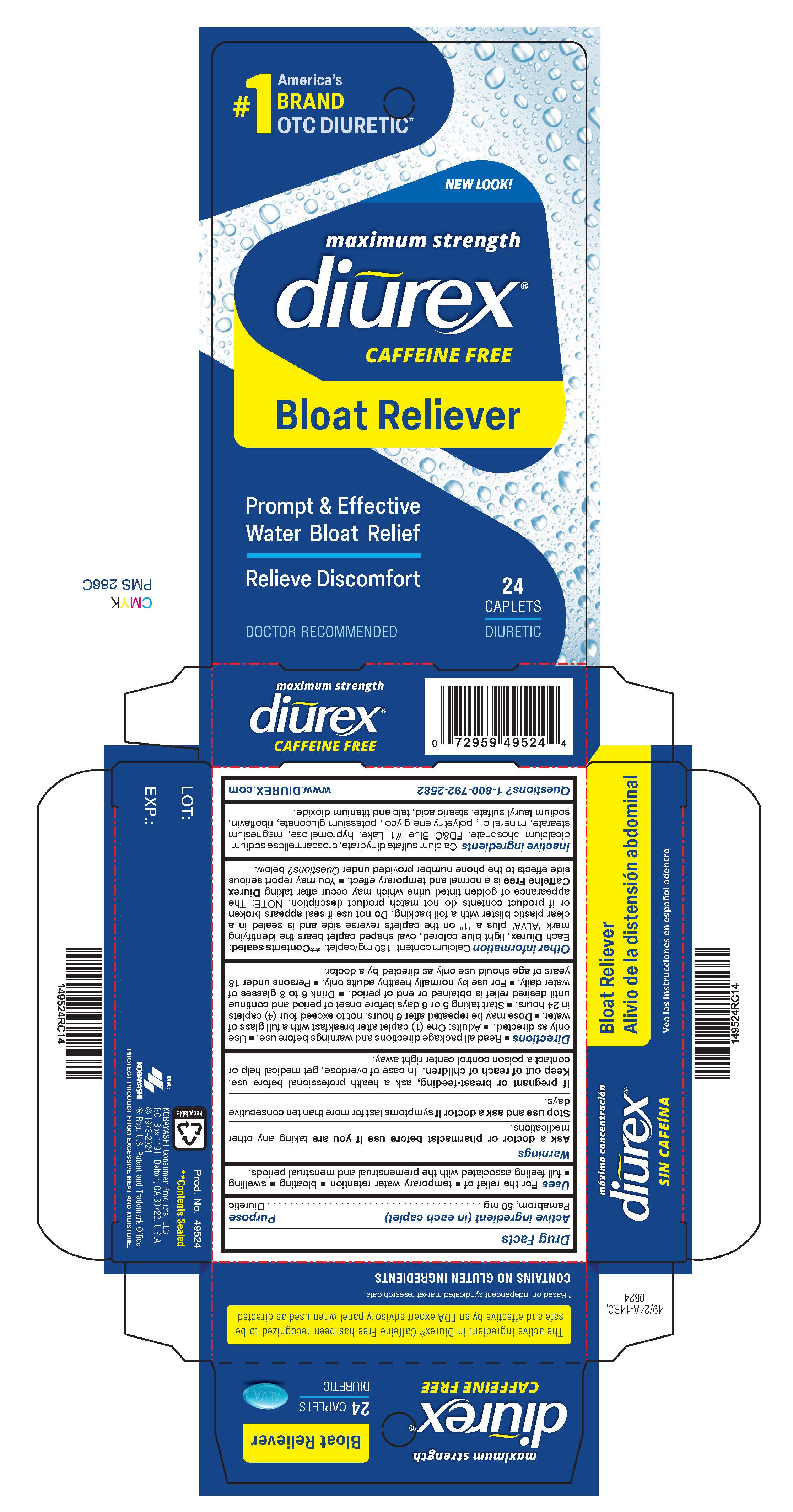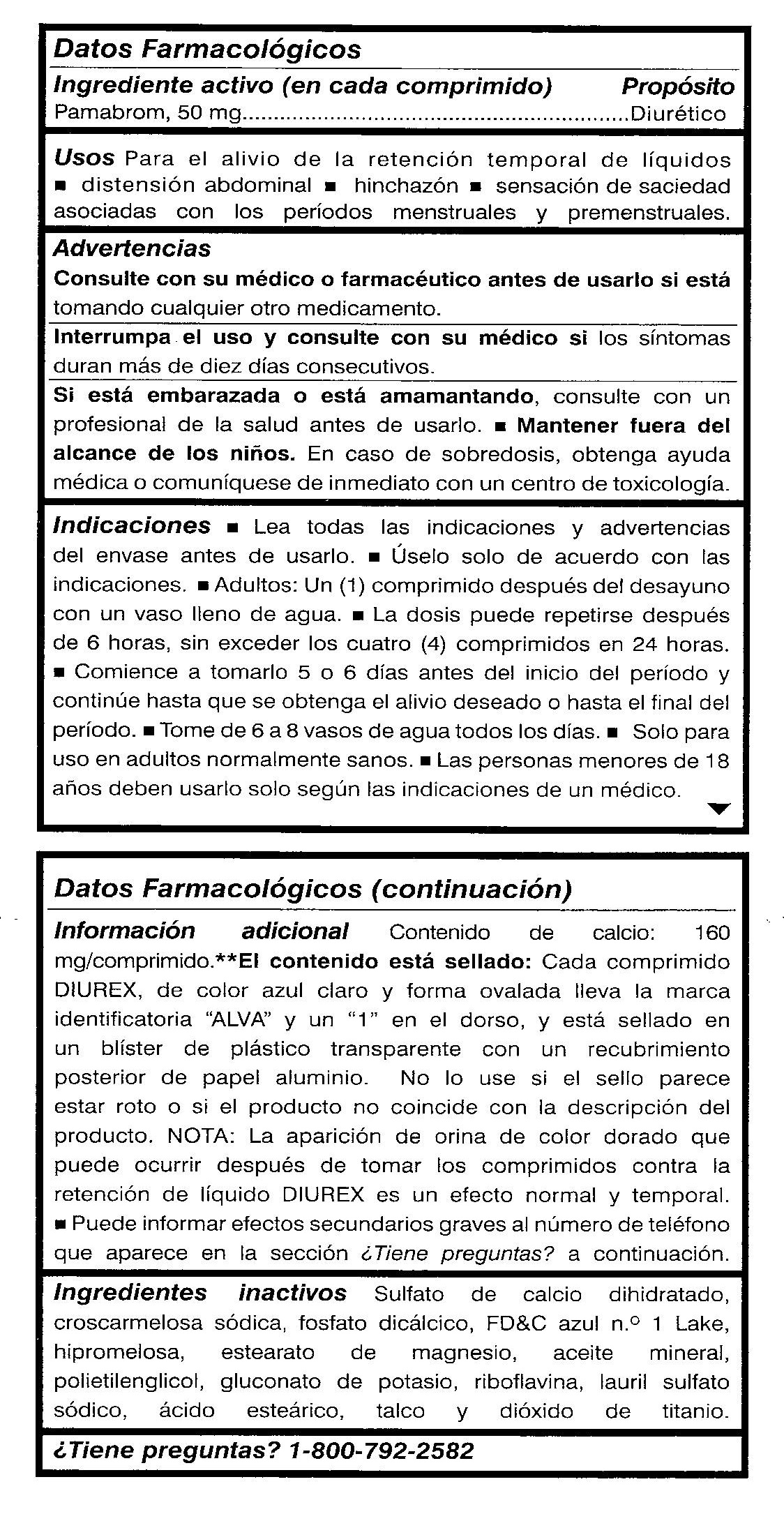 DRUG LABEL: Diurex
NDC: 52389-249 | Form: TABLET, FILM COATED
Manufacturer: Kobayashi Healthcare International, Inc.
Category: otc | Type: HUMAN OTC DRUG LABEL
Date: 20250411

ACTIVE INGREDIENTS: PAMABROM 50 mg/1 1
INACTIVE INGREDIENTS: CROSCARMELLOSE SODIUM; DIBASIC CALCIUM PHOSPHATE DIHYDRATE; FD&C BLUE NO. 1; HYPROMELLOSES; MAGNESIUM STEARATE; LIGHT MINERAL OIL; POLYETHYLENE GLYCOL 400; POTASSIUM GLUCONATE; CALCIUM SULFATE DIHYDRATE; RIBOFLAVIN; SODIUM LAURYL SULFATE; STEARIC ACID; TITANIUM DIOXIDE; TALC

Diurex Max

Active ingredient (in each caplet)

Pamabrom, 50 mg

Purpose

Diuretic

Uses

For the relief of

- temporary water retention
- bloating
- swelling
- full feeling

associated with the premenstrual and menstrual periods.

Warnings

Ask a doctor or pharmacist before use if you are taking any other medications.

Stop use and ask a doctor if symptoms last more than ten consecutive days.

PREGNANCY OR BREAST FEEDING

If pregnant or breastfeeding, ask a health professional before use.

Keep out of reach of children. In case of overdose, get medical help or contact a poison control center right away.

Directions

- Read all package directions and warnings before use.
- Use only as directed.
- Adults: One (1) pill after breakfast with a full glass of water.
- Dose may be repeated after 6 hours, not to exceed four (4) pills in 24 hours.
- Start taking 5 or 6 days before onset of period and continue until desired relief is obtained or end of period.
- Drink 6 to 8 glasses of water daily.
- For use by normally healthy adults only.
- Persons under 18 years of age should use only as directed by a doctor.

Other information

Calcium content: 160 mg/pill. **Contents sealed: Each DIUREX Max, light blue colored, oval shaped pill bears the identifying mark "ALVA" plus a "1" on the pill's reverse side and is sealed in a clear plastic blister with a foil backing. Do not use if seal appears broken or if product contents do not match product description. NOTE: The appearance of golden tinted urine which may occur after taking Diurex Water Pills is a normal and temporary effect. You may report serious side effects to the phone number provided under Questions? below.

Inactive ingredients

Calcium sulfate dihydrate, croscarmellose sodium, dicalcium phosphate, FDC Blue No. 1, hypromellose, magnesium stearate, mineral oil, polyethylene glycol, potassium gluconate, riboflavin, sodium lauryl sulfate, stearic acid, talc and titanium dioxide.

Questions? 1-800-792-2582